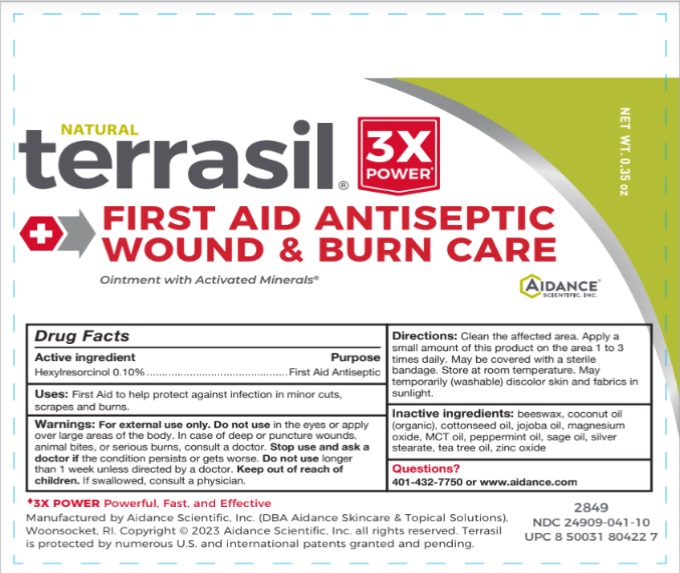 DRUG LABEL: terrasil First Aid Antiseptic Wound and Burn Care
NDC: 24909-041 | Form: OINTMENT
Manufacturer: Aidance Scientific, Inc, DBA Aidance Skincare & Topical Solutions
Category: otc | Type: HUMAN OTC DRUG LABEL
Date: 20250711

ACTIVE INGREDIENTS: HEXYLRESORCINOL 0.1 g/100 g
INACTIVE INGREDIENTS: YELLOW WAX; COCONUT OIL; COTTONSEED OIL; JOJOBA OIL; MAGNESIUM OXIDE; PALM OIL; PEPPERMINT OIL; SAGE OIL; SILVER STEARATE; TEA TREE OIL; ZINC OXIDE

24909-041 terrasil First Aid Antiseptic Wound and Burn Care

Active Ingredient Purpose

Hexylresorcinol 0.10% First Aid Antiseptic

Uses

First Aid to help protect against infection in minor cuts, scrapes, and burns.

Warnings

For external use only.

Do not usein the eyes or apply over large areas of the body. In case of deep or puncture wounds, animal bites, or serious burns, consult a doctor.

Stop use and ask a doctor if the condition persists or gets worse.

Do not use longer than 1 week unless directed by a doctor.

Keep out of reach of children. If swallowed, consult a physician.

Directions

Clean the affected area. Apply a small amount of this product on the area 1 to 3 times daily. May be covered with a sterile bandage.

Inactive Ingredients

beeswax, coconut oil (organic), cottonseed oil, jojoba oil, magnesium oxide, MCT oil, peppermint oil, sage oil, silver stearate, tea tree oil, zinc oxide

Other information

Store at room temperature. May temporarily (washable) discolor skin and fabrics in sunlight.